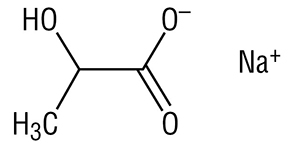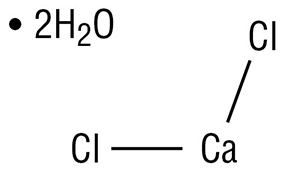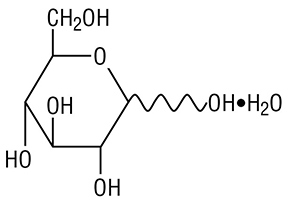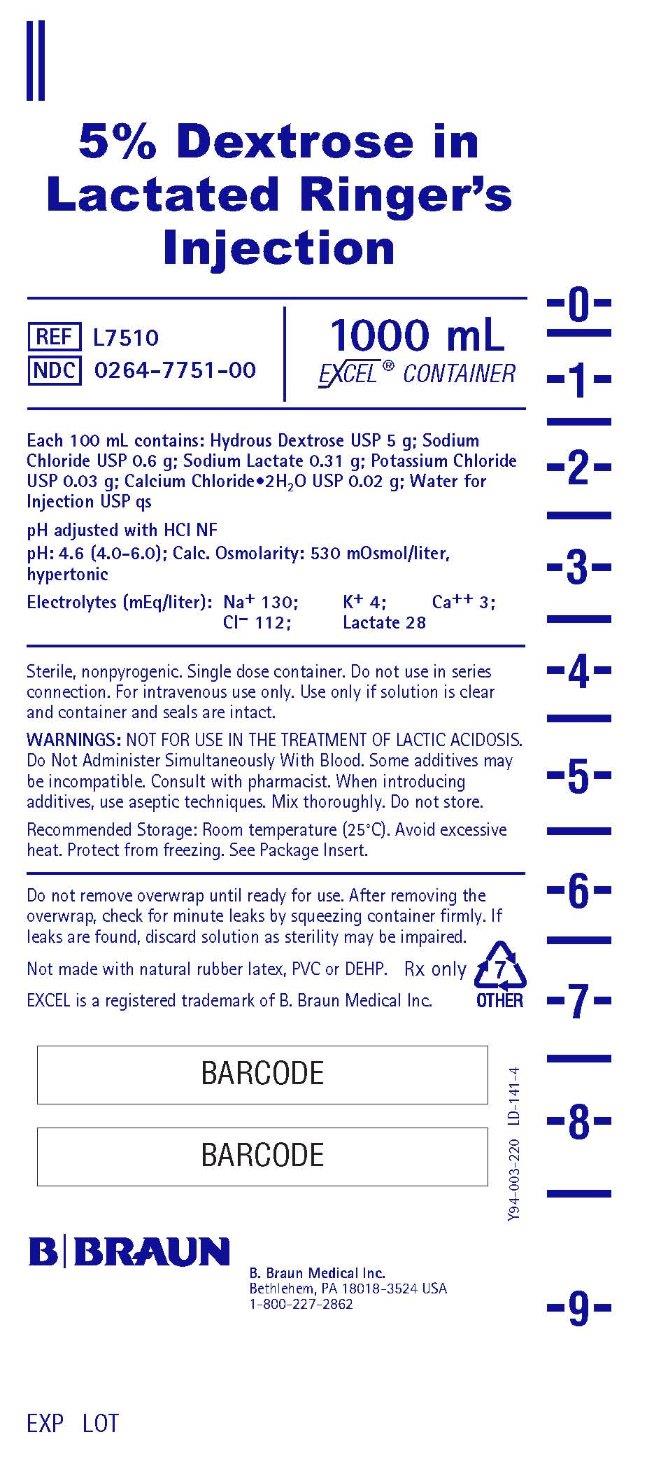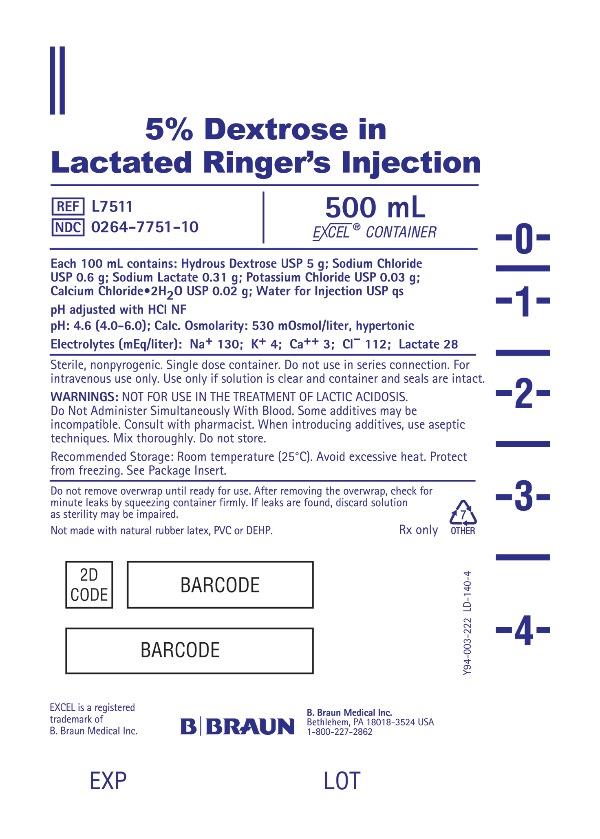 DRUG LABEL: Dextrose in Lactated Ringers
NDC: 0264-7751 | Form: INJECTION, SOLUTION
Manufacturer: B. Braun Medical Inc.
Category: prescription | Type: HUMAN PRESCRIPTION DRUG LABEL
Date: 20251105

ACTIVE INGREDIENTS: DEXTROSE MONOHYDRATE 5 g/100 mL; SODIUM CHLORIDE 0.6 g/100 mL; SODIUM LACTATE 0.31 g/100 mL; POTASSIUM CHLORIDE 0.03 g/100 mL; CALCIUM CHLORIDE 0.02 g/100 mL
INACTIVE INGREDIENTS: WATER

HIGHLIGHTS OF PRESCRIBING INFORMATION

These highlights do not include all the information needed to use LACTATED RINGER’S AND DEXTROSE (5%) INJECTION safely and effectively. See full prescribing information for LACTATED RINGER’S AND DEXTROSE (5%) INJECTION.
LACTATED RINGER’S AND DEXTROSE injection, for intravenous use Initial U.S. Approval: 1971

RECENT MAJOR CHANGES

Dosage and Administration (2.1, 2.2, 2.3, 2.4) 10/2025
Contraindications (4) 10/2025
Warnings and Precautions (5.1, 5.2, 5.3, 5.4, 5.5, 5.6, 5.7, 5.8, 5.9, 5.10, 5.11) 10/2025

1 INDICATIONS AND USAGE

Lactated Ringer’s and Dextrose (5%) Injection is indicated for use as a source of water, electrolytes, and calories or as an alkalinizing agent in adults and pediatric patients.

2 DOSAGE AND ADMINISTRATION

- The recommended dosage and duration are based on the patient’s age, weight, clinical condition, and concomitant therapy. (2.1)
- To reduce the risk of air embolism, adhere to the preparation instructions. (2.2, 5.2)
- Lactated Ringer’s and Dextrose (5%) Injection is for intravenous use (2.3)
- Use a peripheral vein to administer if the final dextrose concentration is 5% or less and the osmolarity is less than 900 mOsm/L. (2.3)
- Consider using a central vein to administer hypertonic solutions with osmolarity of 900 mOsm/L or more to avoid venous irritation, including phlebitis. (2.3)
- Do not administer Lactated Ringer’s and Dextrose (5%) Injection simultaneously with ceftriaxone in neonates (28 days of age or younger) due to serious risks. (2.4)
- See full prescribing information for information dosage considerations, preparation, administration, and drug incompatibilities. (2)

3 DOSAGE FORMS AND STRENGTHS

Injection: Lactated Ringer's and Dextrose (5%) Injection, USP packaged in single-dose EXCEL® containers: 500 mL and 1,000 mL (3)

4 CONTRAINDICATIONS

- Concomitant treatment with ceftriaxone in neonates (28 days of age or younger). (4)
- Patients with known hypersensitivity to sodium lactate. (4)

5 WARNINGS AND PRECAUTIONS

- Serious Risks with Inappropriate Use with Ceftriaxone: Deaths have occurred in neonates (28 days of age or younger) who received concomitant intravenous calcium-containing solutions with ceftriaxone. In patients older than 28 days, ceftriaxone and Lactated Ringer’s and Dextrose (5%) Injection may be administered sequentially if the infusion lines are thoroughly flushed between infusions. (4, 5.1, 8.4)
- Air Embolism: Use a non-vented infusion set or close the vent on a vented set and use a dedicated line without any connections. Pressure infusion is not recommended to increase flow rates, but if necessary, remove all air from the bag prior to initiating infusion. (5.2)
- Hypersensitivity Reactions: Stop the Lactated Ringer’s and Dextrose (5%) Injection infusion immediately if signs or symptoms of a hypersensitivity reaction develop. (5.3)
- Potassium Imbalances, Hyponatremia, Neonatal Hypoglycemia, Hyperglycemic and Hyperosmolar Hyperglycemic State Control, Hypercalcemia, Fluid Overload, Acid-Base Imbalances, Interference with Interpretation of Serum Lactate Levels in Patients with Severe Metabolic Acidosis: See Full Prescribing Information for risk management recommendations. (5.4, 5.5, 5.6, 5.7, 5.8, 5.9, 5.10, 5.11)

6 ADVERSE REACTIONS

Common adverse reactions include infusion site reactions and symptoms of hypersensitivity reactions (e.g., pruritus, dyspnea, urticaria, rash, cough). (6)

To report SUSPECTED ADVERSE REACTIONS, contact B. Braun Medical Inc. at 1-833-425-1464 or FDA at 1-800-FDA-1088 or www.fda.gov/medwatch.

7 DRUG INTERACTIONS

- Drugs that Affect Electrolyte and/or Fluid Balance: Avoid concomitant use. If concomitant use cannot be avoided, closely monitor electrolyte concentrations and fluid balance. (7.1)
- Lithium: Avoid concomitant use. If concomitant use is unavoidable monitor serum lithium concentrations more frequently. (7.2)
- Digoxin: Consider reducing the volume or rate of Lactated Ringer’s and Dextrose (5%) Injection due to the increased risk of digoxin toxicity with calcium-containing solutions. (7.3)
- Drugs with pH-Dependent Renal Elimination: Renal clearance of acidic drugs may be increased. In contrast, renal clearance of alkaline drugs may be decreased. (7.4)

8 USE IN SPECIFIC POPULATIONS

- Closely monitor plasma electrolyte concentrations in young pediatric patients with immature kidney function. (8.4).
- Neonates are at increased risk of developing hypo- or hyperglycemia. Closely monitor to ensure adequate glycemic control. (8.4)
- Geriatric patients are more likely to have decreased renal function. Consider monitoring renal function and starting the infusion at the low end of the dosing range. (8.5)
- Avoid in patients with severe renal impairment. (8.6)
- Patients with severe hepatic impairment may have impaired lactate metabolism. Closely monitor serum lactate levels and acid-base status. (8.7)

FULL PRESCRIBING INFORMATION

1 INDICATIONS AND USAGE

Lactated Ringer’s and Dextrose (5%) Injection is indicated for use as a source of water, electrolytes, and calories or as an alkalinizing agent in adults and pediatric patients.

2 DOSAGE AND ADMINISTRATION

2.1 Dosage Considerations

The recommended dosage and duration of Lactated Ringer’s and Dextrose (5%) Injection is based on the patient’s age, weight, clinical condition, and concomitant therapy. Evaluate the patient’s clinical status and monitor changes in blood glucose and electrolyte concentrations especially during prolonged use of Lactated Ringer’s and Dextrose (5%) Injection to optimize clinical status.

Fluid administration should be based on calculated maintenance or replacement fluid requirements for each patient.

2.2 Important Preparation Instructions

Visually inspect the Lactated Ringer’s and Dextrose (5%) Injection solution for particulate matter and discoloration. Do not administer Lactated Ringer’s and Dextrose (5%) Injection unless the solution is clear and the container seals are intact.

If additives are determined to be compatible with Lactated Ringer’s and Dextrose (5%) Injection then using aseptic technique, mix thoroughly; do not store solutions containing additives. After mixing, do not use if there is discoloration or formation of precipitates.

To reduce the risk of air embolism, adhere to the following Lactated Ringer’s and Dextrose (5%) Injection preparation instructions [see Warnings and Precautions (5.2)]:

- Use a non-vented infusion set or close the vent on a vented set.
- Use a dedicated line without any connections (do not connect flexible containers in series).
- The use of pressure infusion is not recommended as a method to increase flow rates. However, if pressure infusion is required, ensure that any air within the bag is fully evacuated prior to initiation of infusion.
- If using a pumping device to administer Lactated Ringer’s and Dextrose (5%) Injection, turn off the pump before the container is empty.

Preparation Instructions
1. Tear overwrap down at notch and remove solution container. Check for minute leaks by squeezing solution container firmly. If leaks are found, discard solution as sterility may be impaired. If supplemental medication is desired, follow directions below before preparing for administration.
2. Inspect each container. Read the label. Ensure solution is the one ordered and is within the expiration date.
3. Invert container and carefully inspect the solution in good light for cloudiness, haze, or particulate matter. Any container which is suspect should not be used.
4. If supplemental medication is desired, follow directions below [see Dosage and Administration (2.3)].

Preparation for Administration
1. Remove plastic protector from sterile set port at bottom of container.
2. Attach administration set according to its accompanying directions.

2.3 Important Administration Instructions

Lactated Ringer’s and Dextrose (5%) Injection is for intravenous use.

- Use a peripheral vein to administer Lactated Ringer’s and Dextrose (5%) Injection if the final dextrose concentration is 5% or less, and the osmolarity is less than 900 mOsm/L.
- Consider using a central vein to administer hypertonic solutions with osmolarity of 900 mOsm/L or more to avoid venous irritation [see Warnings and Precautions (5.3)].
- It is recommended that intravenous administration apparatus be replaced at least once every 24 hours.

Use immediately after opening the container. Discard the unused portion.

Some additives may be incompatible [see Dosage and Administration (2.4)].

To Add Medication Before Solution Administration
1. Prepare medication site.
2. Using syringe with 18-22 gauge needle, puncture medication port and inner diaphragm and inject.
3. Squeeze and tap ports while ports are upright and mix solution and medication thoroughly.

To Add Medication During Solution Administration
1. Close clamp on the set.
2. Prepare medication site.
3. Using syringe with 18-22 gauge needle of appropriate length (at least 5/8 inch), puncture resealable medication port and inner diaphragm and inject.
4. Remove container from IV pole and/or turn to an upright position.
5. Evacuate both ports by tapping and squeezing them while container is in the upright position.
6. Mix solution and medication thoroughly.
7. Return container to in use position and continue administration.

2.4 Drug Incompatibilities

Do not administer Lactated Ringer’s and Dextrose (5%) Injection simultaneously with ceftriaxone in neonates (28 days of age or younger) due to serious risks [see Contraindications (4) and Warnings and Precautions (5.1)]. However, in patients older than 28 days, ceftriaxone and Lactated Ringer’s and Dextrose (5%) Injection may be administered sequentially if the infusion lines are thoroughly flushed between infusions with a compatible fluid [see Warnings and Precautions (5.1)].

Do not administer Lactated Ringer’s and Dextrose (5%) Injection simultaneously with citrate anticoagulated/preserved blood through the same administration set because of the likelihood of coagulation precipitated by the calcium content of Lactated Ringer’s and Dextrose (5%) Injection.

3 DOSAGE FORMS AND STRENGTHS

Injection: Lactated Ringer's and Dextrose (5%) Injection, USP as a clear, sterile, and nonpyrogenic solution packaged in single-dose EXCEL® containers: 500 mL and 1,000 mL.

4 CONTRAINDICATIONS

Lactated Ringer’s and Dextrose (5%) Injection is contraindicated in:

- Neonates (28 days of age or younger) who are receiving concomitant treatment with ceftriaxone, even if separate infusion lines are used, due to the risk of fatal ceftriaxone-calcium salt precipitation in the neonate’s bloodstream [see Warnings and Precautions (5.1) and Specific Populations (8.4)].
- Patients with known hypersensitivity to any components of Lactated Ringer’s and Dextrose (5%) Injection [see Warnings and Precautions (5.3)].
- Patients with clinically significant hyperglycemia [see Warnings and Precautions (5.7)].

5 WARNINGS AND PRECAUTIONS

5.1 Serious Risk with Concomitant Use with Ceftriaxone

Precipitation of ceftriaxone-calcium can occur when ceftriaxone is mixed with calcium-containing solutions, such as Lactated Ringer’s and Dextrose (5%) Injection, in the same intravenous administration line. Deaths have occurred in neonates (28 days of age or younger) who received concomitant intravenous calcium-containing solutions with ceftriaxone resulting from calcium-ceftriaxone precipitates in the lungs and kidneys, even when separate infusion lines were used.

Lactated Ringer’s and Dextrose (5%) Injection is contraindicated in neonates who receive ceftriaxone [see Contraindications (4), Use in Specific Populations (8.4)]. However, in patients older than 28 days, ceftriaxone and Lactated Ringer’s and Dextrose (5%) Injection may be administered sequentially if the infusion lines are thoroughly flushed between infusions with a compatible fluid.

5.2 Air Embolism

Cases of air embolism have been reported with pressurized administration of intravenous fluids. Air embolism may result in stroke, organ ischemia and/or infarction, and death.

Use a non-vented infusion set or close the vent on a vented set and use a dedicated line without any connections.

If administration is controlled by a pumping device, care must be taken to discontinue the pumping action before the container is empty.

Pressure infusion is not recommended to increase flow rates, but if necessary, ensure all air is removed from the bag before infusion.

Refrain from applying excessive pressure (>300mmHg) causing distortion to the container such as wringing or twisting. Such handling could result in breakage of the container [see Dosage and Administration (2.2)].

5.3 Hypersensitivity Reactions

Hypersensitivity reactions, including anaphylaxis and angioedema, have been reported with Lactated Ringer’s and Dextrose (5%) Injection. Stop the Lactated Ringer’s and Dextrose (5%) Injection infusion immediately and treat patient accordingly if signs or symptoms of a hypersensitivity reaction develop. Initiate appropriate treatment as clinically indicated.

5.4 Potassium Imbalances

Hyperkalemia

Potassium-containing solutions, including Lactated Ringer’s and Dextrose (5%) Injection, may increase the risk of hyperkalemia. This risk is increased in patients predisposed to hyperkalemia including those with severe renal impairment, acute dehydration, extensive tissue injury or burns, heart failure, or in those using concomitant drugs that are associated with hyperkalemia.

Avoid use of Lactated Ringer’s and Dextrose (5%) Injection in patients with, or at increased risk for, hyperkalemia. If use cannot be avoided in these patients, closely monitor serum potassium concentrations.

Hypokalemia

The potassium concentration in Lactated Ringer’s and Dextrose (5%) Injection is similar to the concentration in plasma. It is insufficient to normalize the serum potassium in patients with severe hypokalemia.

5.5 Hyponatremia

Lactated Ringer’s and Dextrose (5%) Injection may cause hyponatremia. Hyponatremia can lead to acute hyponatremic encephalopathy characterized by headache, nausea, seizures, lethargy and vomiting. The risk of hospital-acquired hyponatremia is increased in younger pediatric patients, geriatric patients, patients treated with diuretics, and patients with cardiac or pulmonary failure or with the syndrome of inappropriate antidiuretic hormone (SIADH) (e.g., postoperative patients, patients concomitantly treated with arginine vasopressin analogs, or certain antiepileptic, psychotropic, or cytotoxic drugs) [see Drug Interactions (7.1), Use in Specific Populations (8.4)].

Avoid Lactated Ringer’s and Dextrose (5%) Injection in patients with or at risk for hyponatremia. If use cannot be avoided in these patients, closely monitor serum sodium concentrations.

Rapid correction of hyponatremia may result in serious neurologic complications such as osmotic demyelination syndrome (ODS). To avoid complications, monitor serum sodium and chloride concentrations, fluid status, acid-base balance, and neurologic status.

5.6 Neonatal Hypoglycemia

Neonates, especially preterm neonates with low birth weight, are at increased risk of developing hypoglycemia. Closely monitor blood glucose concentration during treatment with intravenous dextrose solutions to ensure adequate glycemic control in order to avoid potential long-term adverse effects.

5.7 Hyperglycemia and Hyperosmolar Hyperglycemic State

Administration of solutions containing dextrose and lactate in patients with impaired glucose tolerance including those with diabetes mellitus may worsen hyperglycemia. Hyperglycemia is associated with an increase in serum osmolality, which can result in hypovolemia and electrolyte imbalances due to osmotic diuresis.

Patients with underlying central nervous system disease or renal impairment who receive dextrose infusions may be at greater risk of developing hyperosmolar hyperglycemic state.

While using Lactated Ringer’s and Dextrose (5%) Injection, closely monitor blood glucose concentrations and treat hyperglycemia to maintain glucose concentrations within normal limits. Anti-diabetic drugs may need to be started or dosages of these drugs may need to be increased to maintain optimal blood glucose concentrations.

5.8 Hypercalcemia

Lactated Ringer’s and Dextrose (5%) Injection contains calcium salts and may cause hypercalcemia. Avoid administration of Lactated Ringer’s and Dextrose (5%) Injection in patients with hypercalcemia, those with calcium-containing renal calculi or history of such calculi, or those with conditions predisposing to hypercalcemia or treated with concomitant thiazide diuretics or vitamin D.

5.9 Fluid Overload

Depending on the administered volume and the infusion rate, administration of Lactated Ringer’s and Dextrose (5%) Injection can cause fluid overload, including pulmonary edema.

Avoid Lactated Ringer’s and Dextrose (5%) Injection in patients at risk for fluid and/or solute overload including patients with severe renal impairment. If use cannot be avoided in these patients, monitor fluid balance, electrolyte concentrations and acid base balance, especially during prolonged use.

5.10 Acid/Base Imbalances

Because lactate is metabolized to bicarbonate, administration of Lactated Ringer’s and Dextrose (5%) Injection may result in, or worsen, metabolic alkalosis. Closely monitor the acid-base balance in patients with, or at risk of, alkalosis.

In patients with severe hepatic impairment, decreased lactate metabolism may result in worsening anion gap metabolic acidosis. Avoid Lactated Ringer’s and Dextrose (5%) Injection in patients with severe hepatic impairment. If use cannot be avoided in these patients, closely monitor serum bicarbonate levels.

5.11 Interference of Lactated Ringer’s and Dextrose (5%) Injection with Interpretation of Serum Lactate Levels in Patients with Severe Metabolic Acidosis

Administration of Lactated Ringer’s and Dextrose (5%) Injection may result in interference with the interpretation of serum lactate levels in patients with severe metabolic acidosis. [see Drug Interactions (7.5)].

6 ADVERSE REACTIONS

The following serious adverse reactions are discussed in greater detail in other sections of the labeling:

- Serious Risk with Concomitant Use with Ceftriaxone [see Warnings and Precautions (5.1)]
- Air Embolism [see Warnings and Precautions (5.2)]
- Hypersensitivity Reactions [see Warnings and Precautions (5.3)]
- Potassium Imbalances [see Warnings and Precautions (5.4)]
- Hyponatremia [see Warnings and Precautions (5.5)]
- Neonatal Hypoglycemia [see Warnings and Precautions (5.6)]
- Hyperglycemia and Hyperosmolar Hyperglycemic State [see Warnings and Precautions (5.7)]
- Hypercalcemia [see Warnings and Precautions (5.8)]
- Fluid Overload [see Warnings and Precautions (5.9)]
- Acid/Base Imbalances [see Warnings and Precautions (5.10)]

The following adverse reactions have been identified during post approval use of Lactated Ringer’s Products. Because these reactions are reported voluntarily from a population of uncertain size, it is not always possible to reliably estimate their frequency or establish a causal relationship to drug exposure:

General Disorders and Administration Site Conditions:
Phlebitis, extravasation, infusion site inflammation, infusion site swelling, infusion site rash, infusion site pruritus, infusion site erythema, infusion site pain, infusion site burning, and infusion site hypoaesthesia.

Hypersensitivity Reactions and Infusion Reactions:
Angioedema, chest pain/discomfort, bradycardia or tachycardia, hypotension, respiratory distress, bronchospasm, dyspnea, cough, urticaria, rash, pruritus, erythema, flushing, throat irritation, paresthesia, oral hypoesthesia, dysgeusia, nausea, anxiety, pyrexia, and headache, laryngeal edema, sneezing, and injection site infection.

Metabolism and Nutrition Disorders:
Hyperkalemia, hyponatremia, and hypervolemia.

Nervous System Disorders:
Hyponatremic encephalopathy.

7 DRUG INTERACTIONS

7.1 Drugs that Affect Electrolyte and/or Fluid Balance

Hyperkalemia

Administration of Lactated Ringer’s and Dextrose (5%) Injection to patients concomitantly treated or recently treated with drugs that are associated with hyperkalemia increases the risk of severe and potentially fatal hyperkalemia, especially in the presence of other hyperkalemia risk factors. Avoid use of Lactated Ringer’s and Dextrose (5%) Injection in patients receiving drugs that are associated with hyperkalemia (e.g., potassium-sparing diuretics, ACE inhibitors, angiotensin II receptor antagonists, or calcineurin inhibitors). If concomitant use cannot be avoided, closely monitor serum potassium concentrations during concomitant use [see Warnings and Precautions (5.4)].

Hyponatremia

Administration of Lactated Ringer’s and Dextrose (5%) Injection to patients treated concomitantly with drugs associated with hyponatremia may increase the risk of developing hyponatremia. These drugs include diuretics and those that cause SIADH (e.g., arginine vasopressin analogs, certain antiepileptic, psychotropic, or cytotoxic drugs). Avoid use of Lactated Ringer’s and Dextrose (5%) Injection in patients receiving such drugs. If use cannot be avoided, closely monitor serum sodium concentrations during concomitant use [see Warnings and Precautions (5.5)].

Hypercalcemia

Avoid the use of Lactated Ringer’s and Dextrose (5%) Injection in patients treated with thiazide diuretics or vitamin D because these drugs can increase the risk of hypercalcemia. If use cannot be avoided, closely monitor serum calcium concentrations during concomitant use [see Warnings and Precautions (5.8)].

Hypernatremia and Fluid Retention

Administration of Lactated Ringer’s and Dextrose (5%) Injection to patients treated concomitantly with drugs associated with sodium and fluid retention (e.g., corticosteroids or corticotropin) may increase the risk of hypernatremia and volume overload. Avoid use of Lactated Ringer’s and Dextrose (5%) Injection in patients receiving such drugs. If use cannot be avoided, closely monitor serum electrolytes, fluid balance, and acid-base balance during concomitant use.

7.2 Lithium

Renal sodium and lithium clearance may be increased during concomitant use of Lactated Ringer’s and Dextrose (5%) Injection and lithium and may result in decreased lithium concentrations. Avoid use of Lactated Ringer’s and Dextrose (5%) Injection in patients receiving lithium. If use cannot be avoided, increase the frequency of monitoring of serum lithium concentrations during concomitant use.

7.3 Digoxin

Administration of calcium via use of Lactated Ringer’s and Dextrose (5%) Injection may increase digoxin’s effects and lead to digoxin toxicity including serious or fatal cardiac arrhythmias. In digoxin-treated patients, consider reducing the volume and/or rate of Lactated Ringer’s and Dextrose (5%) Injection administration.

7.4 Drugs with pH-Dependent Renal Elimination

Due to the alkalinizing action of lactate (formation of bicarbonate), Lactated Ringer’s and Dextrose (5%) Injection may interfere with the elimination of drugs with pH-dependent renal elimination. Renal clearance of alkaline drugs may be decreased. In contrast, renal clearance of acidic drugs may be increased.

7.5 Interference of Lactated Ringer’s and Dextrose (5%) Injection with Interpretation of Serum Lactate Levels in Patients with Severe Metabolic Acidosis

Because administration of Lactated Ringer’s and Dextrose (5%) Injection may interfere with the interpretation of serum lactate levels in patients with severe metabolic acidosis; assessment of the patient’s clinical status should not solely rely on the measurement of serum lactate.

8 USE IN SPECIFIC POPULATIONS

8.1 Pregnancy

Risk Summary

Lactated Ringer’s as a source of water and electrolytes has been used for decades during labor and delivery. Although there are no reports of use of Lactated Ringer’s in other stages of pregnancy, exposure during pregnancy is not expected to cause major birth defects, miscarriage, or adverse maternal or fetal outcomes. Animal reproduction studies have not been conducted with this drug.

The background risk of major birth defects and miscarriage for the indicated population is unknown. All pregnancies have a background risk of birth defect, loss, or other adverse outcomes. In the U.S. general population, the estimated background risk of major birth defects and miscarriage in clinically recognized pregnancies is 2 to 4% and 15 to 20%, respectively.

8.2 Lactation

Risk Summary

Lactated Ringer’s as a source of water and electrolytes and Dextrose Injection (5%) have been used for decades and is not expected to cause harm to a breastfed infant. There are no data on the presence of Lactated Ringer’s and Dextrose (5%) Injection in human milk, the effects on the breastfed infant, or the effects on milk production. The developmental and health benefits of breastfeeding should be considered along with the mother’s clinical need for Lactated Ringer’s and Dextrose (5%) Injection and any potential adverse effects on the breastfed infant from Lactated Ringer’s and Dextrose (5%) Injection or from the underlying maternal condition.

8.4 Pediatric Use

Lactated Ringer’s and Dextrose (5%) Injection is contraindicated in neonates (28 days of age or younger) who are receiving ceftriaxone due to reported deaths that occurred when neonates received ceftriaxone and intravenous calcium-containing solutions concomitantly [see Warnings and Precautions (5.1)].

The safety and effectiveness of Lactated Ringer’s Injection for use as a source of water, electrolytes, and calories or as an alkalinizing agent have been established in pediatric patients of all ages, including neonates.

Closely monitor plasma electrolyte concentrations in young pediatric patients with immature kidney function who may have decreased ability to maintain fluid and electrolyte balance [see Warnings and Precautions (5.4, 5.5, 5.8, 5.9)]. Administration of a lactate-containing intravenous solution, including Lactated Ringer’s and Dextrose (5%) Injection to pediatric patients should account for liver and kidney maturation (the kidney function affects the biotransformation and renal excretion of lactate [see Warnings and Precautions (5.9)]. Pediatric patients are at increased risk for developing hyponatremic encephalopathy [see Warnings and Precautions (5.5)].

Neonates, especially preterm neonates with low birth weight, are at increased risk of developing hypo- or hyperglycemia and therefore need close monitoring during treatment with intravenous glucose solutions including Lactated Ringer’s and Dextrose (5%) Injection to ensure adequate glycemic control to avoid potential long-term adverse reactions [see Warnings and Precautions (5.6, 5.7)]. In very low birth weight neonates, excessive or rapid administration of Lactated Ringer’s and Dextrose (5%) Injection may result in increased serum osmolality and risk of intracranial hemorrhage.

8.5 Geriatric Use

Geriatric patients treated with Lactated Ringer’s and Dextrose (5%) Injection are at increased risk of developing electrolyte imbalances. Lactated Ringer’s and Dextrose (5%) Injection is substantially excreted by the kidney, and the risk of adverse reactions to Lactated Ringer’s and Dextrose (5%) Injection may be greater in patients with renal impairment than in patients with normal renal function. Because geriatric patients are more likely to have decreased renal function, consider monitoring renal function in geriatric patients and consider starting the infusion at the low end of the dosing range.

8.6 Renal Impairment

Administration of Lactated Ringer’s and Dextrose (5%) Injection to patients with or at risk of severe renal impairment, may result in hyperkalemia and/or fluid overload [see Warnings and Precautions (5.4, 5.7, 5.9)]. Avoid Lactated Ringer’s and Dextrose (5%) Injection in patients with severe renal impairment. If use cannot be avoided in such patients, monitor for development of these adverse reactions.

8.7 Hepatic Impairment

In patients with severe hepatic impairment, lactate metabolism may be impaired and Lactated Ringer’s and Dextrose (5%) Injection may not produce alkalinization. Closely monitor serum lactate levels and acid-base status in such patients.

10 OVERDOSAGE

Excessive administration of Lactated Ringer’s and Dextrose (5%) Injection can cause:

- Hyperkalemia and hypernatremia, especially in patients with severe renal impairment.
- Fluid overload (which can lead to pulmonary and/or peripheral edema).
- Hyperglycemia, hyperosmolarity, and osmotic diuresis, dehydration, and electrolyte loss.
- Metabolic alkalosis with or without hypokalemia.
- Loss of bicarbonate with an acidifying effect
- Hypercalcemia

Overdose interventions include Lactated Ringer’s and Dextrose (5%) Injection discontinuation, treatment of hyperkalemia, treatment of hyperglycemia, and close monitoring of fluid balance, electrolyte concentrations, and acid-base balance [see Warnings and Precautions (5.4, 5.5, 5.6, 5.7, 5.8, 5.9, 5.10)].

11 DESCRIPTION

Lactated Ringer’s and Dextrose (5%) Injection USP is a sterile, nonpyrogenic solution for fluid and electrolyte replenishment and caloric supply in a single-dose container for intravenous administration.

Composition, osmolarity, pH, ionic concentration and caloric content are shown in Table 1. Dextrose is derived from corn.

Table 1

 | Size (mL) | Composition (g/L) |  |  |  |  | Osmolarity [Normal physiologic osmolarity range is approximately 280 to 310 mOsmol/L.] (mOsmol/L) (calc) | pH [pH adjusted with Hydrochloric Acid NF.] | Ionic Concentration (mEq/L) |  |  |  | Lactate | Caloric Content (kcal/L)
 | Size (mL) | Dextrose, USP | Sodium Chloride, USP | Sodium Lactate | Potassium Chloride, USP | Calcium Chloride, USP | Osmolarity [Normal physiologic osmolarity range is approximately 280 to 310 mOsmol/L.] (mOsmol/L) (calc) | pH [pH adjusted with Hydrochloric Acid NF.] | Sodium | Potassium | Calcium | Chloride | Lactate | Caloric Content (kcal/L)
Lactated Ringer’s and Dextrose (5%) Injection, USP | 500 1000 | 50 | 6 | 3.1 | 0.3 | 0.2 | 530 | 4.6 (4.0 to 6.0) | 130 | 4 | 3 | 112 | 28 | 180

The chemical name, structural formula, and molecular weight of the active ingredients are shown in Table 2.

Table 2

Ingredients | Molecular Formula | Molecular Weight
Sodium Chloride USP | Na^+ Cl^– | 58.44
Sodium Lactate |  | 112.06
Potassium Chloride USP | K^+ Cl^– | 74.55
Calcium Chloride Dihydrate USP |  | 147.02
Dextrose USP |  | 198.17

Not made with natural rubber latex, PVC or DEHP.

The plastic container is made from a multilayered film developed for parenteral drugs. It contains no plasticizers and has minimal leachables. The solution contact layer is a rubberized copolymer of ethylene and propylene. The container-solution unit is a closed system and is not dependent upon entry of external air during administration. The container is overwrapped to provide protection from the physical environment and to provide an additional moisture barrier when necessary.

The closure system has two ports; the one for the administration set has a tamper evident plastic protector and the other is a medication addition site [see Dosage and Administration (2.3)].

12 CLINICAL PHARMACOLOGY

12.1 Mechanism of Action

Lactated Ringer’s and Dextrose (5%) Injection is a source of water, electrolytes, and calories, and produces an alkalinizing effect.

- Sodium, the major cation of the extracellular fluid, functions primarily in the control of water distribution, fluid balance, and osmotic pressure of body fluids. Sodium is also associated with chloride and bicarbonate in the regulation of the acid-base equilibrium of body fluid.
- Potassium, the principal cation of intracellular fluid, participates in carbohydrate utilization and protein synthesis, and is critical in the regulation of nerve conduction and muscle contraction, particularly in the heart.
- Chloride, the major extracellular anion, closely follows the metabolism of sodium, and changes in the acid-base balance of the body are reflected by changes in the chloride concentration.
- Calcium, an important cation, provides the framework of bones and teeth in the form of calcium phosphate and calcium carbonate. In the ionized form, calcium is essential for the functional mechanism of the clotting of blood, normal cardiac function, and regulation of neuromuscular irritability.
- Sodium lactate provides sodium and lactate ions. The lactate anion is in equilibrium with pyruvate and has an alkalinizing effect resulting from simultaneous removal by the liver of lactate and hydrogen ions. The sodium ion combines with bicarbonate ion produced from carbon dioxide of the body and thus retains bicarbonate to combat metabolic acidosis (bicarbonate deficiency).
- Dextrose provides a source of calories. Dextrose may decrease losses of body protein and nitrogen, promotes glycogen deposition and decreases or prevents ketosis if sufficient doses are provided.

12.2 Pharmacodynamics

The exposure-response relationship and time course of pharmacodynamic response for the safety and effectiveness of Lactated Ringer’s and Dextrose (5%) Injection have not been fully characterized.

12.3 Pharmacokinetics

Elimination

Metabolism/Excretion

Potassium: Normally about 80 to 90% of the potassium intake is excreted in the urine; the remainder is excreted in feces and to a smaller extent, in perspiration.

Sodium and Chloride: The distribution and excretion of sodium (Na^+) and chloride (Cl^−) are largely under the control of the kidney which maintains a balance between intake and output.

Lactate: In the liver, lactate is metabolized to carbon dioxide and water by oxidative metabolism and consumption of hydrogen cations.

Dextrose: Dextrose injected parenterally undergoes oxidation to carbon dioxide and water.

13 NONCLINICAL TOXICOLOGY

13.1 Carcinogenesis, Mutagenesis, Impairment of Fertility

Carcinogenicity, genetic toxicology, and animal fertility studies have not been conducted with Lactated Ringer’s and Dextrose (5%) Injection.

16 HOW SUPPLIED/STORAGE AND HANDLING

How Supplied

Lactated Ringer’s and Dextrose (5%) Injection USP is supplied sterile and nonpyrogenic in single-dose EXCEL® Containers. The 1000 mL containers are packaged 12 per case, the 500 mL containers are packaged 24 per case.

It is available in the following presentations:

NDC | REF | Size
0264-7751-00 | L7510 | 1000 mL
0264-7751-10 | L7511 | 500 mL

Storage and Handling

Store at 20°C to 25°C (68°F to 77°F); excursions permitted between 15°C to 30°C (59°F to 86°F). [See USP Controlled Room Temperature.] Minimize exposure of Lactated Ringer’s and Dextrose (5%) Injection to heat. Avoid excessive heat. Protect from freezing.

EXCEL is a registered trademark of B. Braun Medical Inc.

Rx only

B. Braun Medical Inc.
Bethlehem, PA 18018-3524 USA
1-800-227-2862

Y36-003-100 LD-380-7

PRINCIPAL DISPLAY PANEL - 1000 mL Container Label

5% Dextrose in
Lactated Ringer's
Injection
REF L7510
NDC 0264-7751-00

1000 mL
EXCEL® CONTAINER

Each 100 mL contains: Hydrous Dextrose USP 5 g; Sodium
Chloride USP 0.6 g; Sodium Lactate 0.31 g; Potassium Chloride
USP 0.03 g; Calcium Chloride•2H2O USP 0.02 g; Water for
Injection USP qs

pH adjusted with HCl NF
pH: 4.6 (4.0-6.0); Calc. Osmolarity: 530 mOsmol/liter,
hypertonic

Electrolytes (mEq/liter): Na^+ 130; K^+ 4; Ca^++ 3;
Cl^– 112; Lactate 28

Sterile, nonpyrogenic. Single dose container. Do not use in series
connection. For intravenous use only. Use only if solution is clear
and container and seals are intact.

WARNINGS: NOT FOR USE IN THE TREATMENT OF LACTIC ACIDOSIS.

Do Not Administer Simultaneously With Blood. Some additives may
be incompatible. Consult with pharmacist. When introducing
additives, use aseptic techniques. Mix thoroughly. Do not store.

Recommended Storage: Room temperature (25°C). Avoid excessive
heat. Protect from freezing. See Package Insert.

Do not remove overwrap until ready for use. After removing the
overwrap, check for minute leaks by squeezing container firmly. If
leaks are found, discard solution as sterility may be impaired.

Not made with natural rubber latex, PVC or DEHP.

Rx only

EXCEL is a registered trademark of B. Braun Medical Inc.

B. Braun Medical Inc.
Bethlehem, PA 18018-3524 USA
1-800-227-2862

Y94-003-220 LD-141-4

EXP
LOT

PRINCIPAL DISPLAY PANEL - 500 mL Container Label

5% Dextrose in
Lactated Ringer's Injection

REF L7511
NDC 0264-7751-10

500 mL
EXCEL® CONTAINER
Each 100 mL contains: Hydrous Dextrose USP 5 g; Sodium Chloride
USP 0.6 g; Sodium Lactate 0.31 g; Potassium Chloride USP 0.03 g;
Calcium Chloride•2H2O USP 0.02 g; Water for Injection USP qs

pH adjusted with HCl NF
pH: 4.6 (4.0-6.0); Calc. Osmolarity: 530 mOsmol/liter,
hypertonic

Electrolytes (mEq/liter): Na^+ 130; K^+ 4; Ca^++ 3;
Cl^– 112; Lactate 28

Sterile, nonpyrogenic. Single dose container. Do not use in series
connection. For intravenous use only. Use only if solution is clear
and container and seals are intact.

WARNINGS: NOT FOR USE IN THE TREATMENT OF LACTIC ACIDOSIS.

Do Not Administer Simultaneously With Blood. Some additives may
be incompatible. Consult with pharmacist. When introducing
additives, use aseptic techniques. Mix thoroughly. Do not store.

Recommended Storage: Room temperature (25°C). Avoid excessive
heat. Protect from freezing. See Package Insert.

Do not remove overwrap until ready for use. After removing the
overwrap, check for minute leaks by squeezing container firmly. If
leaks are found, discard solution as sterility may be impaired.

Not made with natural rubber latex, PVC or DEHP.

Rx only

EXCEL is a registered trademark of B. Braun Medical Inc.

B. Braun Medical Inc.
Bethlehem, PA 18018-3524 USA
1-800-227-2862

Y94-003-222
LD-140-4

EXP
LOT